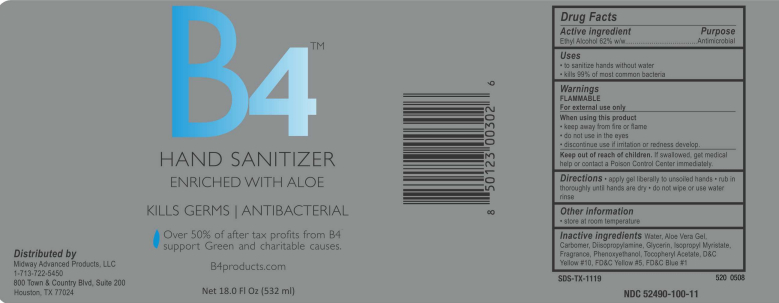 DRUG LABEL: B4 
NDC: 52490-100 | Form: GEL
Manufacturer: Midway Advanced Products, LLC
Category: otc | Type: HUMAN OTC DRUG LABEL
Date: 20110324

ACTIVE INGREDIENTS: Alcohol 42 mg/25 mL
INACTIVE INGREDIENTS: Water; ALOE VERA LEAF; CARBOMER HOMOPOLYMER TYPE C; Diisopropylamine; Glycerin; Isopropyl Myristate; Phenoxyethanol; D&C YELLOW NO. 10; FD&C YELLOW NO. 5; FD&C BLUE NO. 1

Drug Facts

Active ingredient

Ethyl Alcohol 62% w/w

Purpose

Antimicrobial

Uses

- To sanitize hands without water.
- Kills 99% of most common bacteria.

Warnings

FLAMMABLE

For external use only.

When using this product

- keep away from fire or flame.
- do not use in the eyes.
- discontinue use if irritation or redness develop.

Keep out of reach of children.

If swallowed, get medical help or contact a Poison Control Center immediately.

Directions

- apply gel liberally to unsoiled hands.
- rub in thoroughly until hands are dry.
- do not wipe or use water rinse.

Other information

- Store at room temperature.

Inactive ingredients

Water, Aloe Vera Gel, Carbomer, Diisopropylamine, Glycerin, Isopropyl Myristate, Fragrance, Phenoxyethanol, Tocopheryl Acetate, D and C Yellow #10, FD and C Yellow #5, FD and C Blue #1

Distributed by

Midway Advanced Products, LLC
1-713-629-5200
800 Town and Country Blvd, Suite 200, Houston, TX 77024

Principal Display Panel

B4

HAND SANITIZER
ENRICHED WITH ALOE
KILLS GERMS | ANTIBACTERIAL
Over 50% of after tax profits from B4
support Green and charitable causes.
B4products.com

Net 18.0 Fl Oz (532 ml)